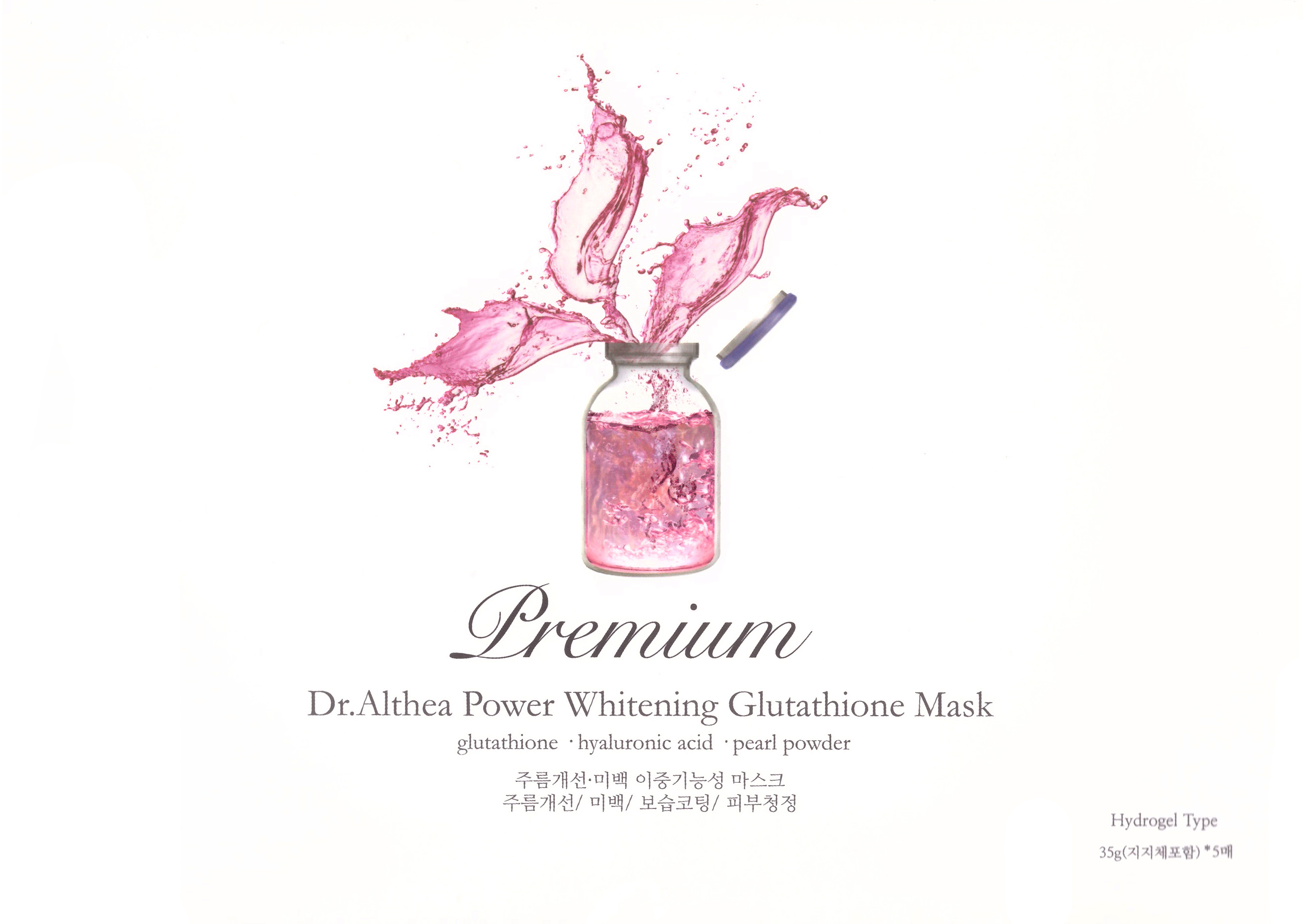 DRUG LABEL: Premium Dr. Althea Power Whitening Glutathione Mask
NDC: 70905-0007 | Form: LIQUID
Manufacturer: Dr. Althea
Category: otc | Type: HUMAN OTC DRUG LABEL
Date: 20160812

ACTIVE INGREDIENTS: NIACINAMIDE 2 g/100 g; ADENOSINE 0.04 g/100 g
INACTIVE INGREDIENTS: WATER; BUTYLENE GLYCOL

Drug Facts

ACTIVE INGREDIENT

Niacinamide, Adenosine

INACTIVE INGREDIENT

Water, Glycerin, Caprylic/Capric Triglyceride, Ceratonia Siliqua Gum, Polysorbate 60, Chondrus Crisps (Carrageenan) Extract, Lactobacillus Ferment, Scutellaria Baicalensis Root Extract, Camellia Sinensis Leaf Extract, Artemisia Princeps Leaf Extract, Houttuynia Cordata Extract, Citrus Junos Fruit Extract, Ricans Communis (Castor) SeedOil, 1,2-Hexanediol, Caprylyl Glycol, Phenoxyethanol, Mica, Titanium Dioxide, Tin Oxide, Allantoin, Panthenol, Ethylhexylglycerin, Disodium EDTA, Fragrance, Butylene Glycol, Sodium Hyaluronate, Hydrolyzed Collagen, Rosa Centifolia Flower Extract, Glycyrrhiza Glabra (Licorice) Root Extract, Coix Lacryma-Jobi Ma-yuen Seed Extract, Leontopodium Alpinum Extract, Alcohol, Propolis Extract, Potassium Hydroxide, Snail Secretion Filtrate, Glutathione(100ppm), Dipotassium Glycyrrhizate, Pearl Powder, Leucojum Aestivum Bulb Extract, Arganil Spinosa Kernel Oil, Simmondsia Chinensis (Jojoba) Seed Oil, Rosa Canina Fruit Oil, Vitis Vinifera (Grape) Seed Oil, Cocos Nucifera (Coconut) Oil

PURPOSE

Helps to fight against wrinkles. Helps skin whitening

keep out of reach of the children

INDICATIONS AND USAGE

Open the pouch and take out a mask. Remove films on the both side and attach to face for 20~40 minutes, then remove the mask.

WARNINGS

1. If the following symptoms occur after product use, stop using the product immediately and consult a dermatologist (continuous use can exacerbate the symptoms).
1) Occurrence of red spots, swelling, itchiness, and other skin irritation
2) If the symptoms above occur after the application area is exposed to direct sunlight
2. Do not use on open wounds, eczema, and other skin irritations
3. Precaution for Storage and Handling
1) Close the lid after use
2) Keep out of reach of infants and children
3) Do not to store in a place with high/low temperature and exposed to direct sunlight

4. Use as avoiding eye areas.

DOSAGE AND ADMINISTRATION

for external use only